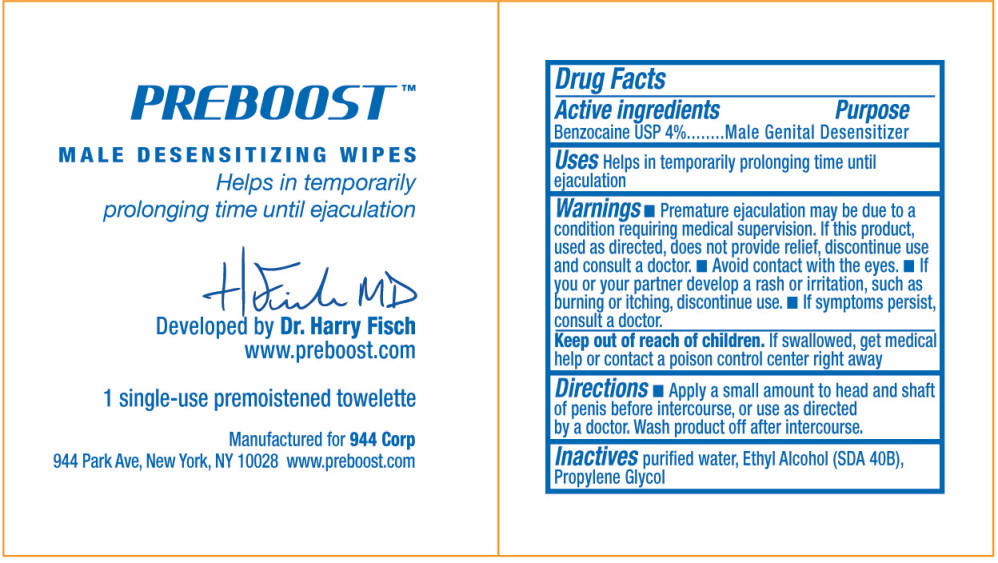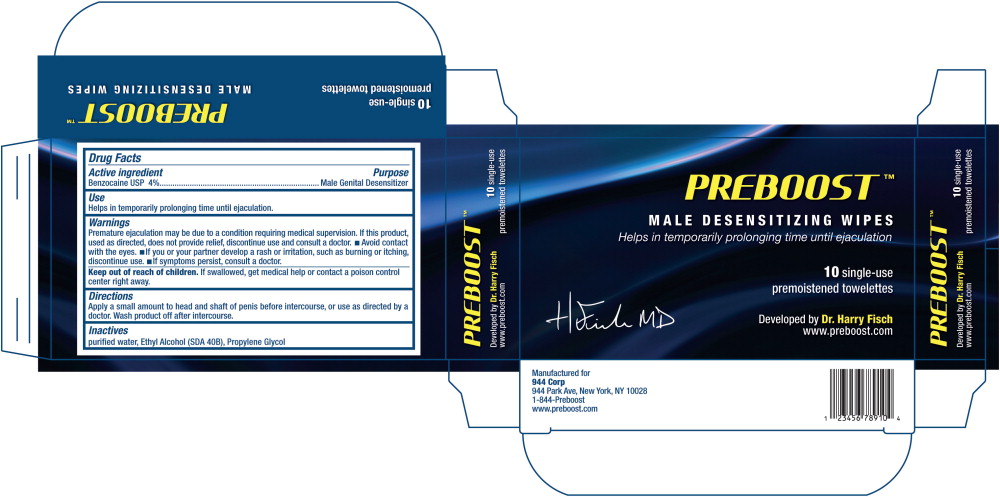 DRUG LABEL: Preboost
NDC: 62192-8500 | Form: LIQUID
Manufacturer: 944 Corp
Category: otc | Type: HUMAN OTC DRUG LABEL
Date: 20140218

ACTIVE INGREDIENTS: benzocaine 4 g/100 mL
INACTIVE INGREDIENTS: alcohol; water; propylene glycol

Male Genital Desensitizer
Towelette

Drug Facts

Active Ingredients

Benzocaine USP 4.0%

Purpose

Male Genital Desensitizer

Use

Helps in temporarily prolonging time until ejaculation.

Warnings

Premature ejaculation may be due to a condition requiring medical supervision. If this product, used as directed, does not provide relief, discontinue use and consult a doctor.

- Avoid contact with the eyes.
- If you or your partner develop a rash or irritation, such as burning or itching, discontinue use.
- If symptoms persist, consult a doctor.

Keep out of reach of children. If swallowed, get medical help or contact a poison control center right away.

Directions

Apply a small amount to head and shaft of penis before intercourse, or use as directed by a doctor. Wash product off after intercourse.

Inactives

purified water, Ethyl Alcohol (SDA 40B), Propylene Glycol

PRINCIPAL DISPLAY PANEL – pouch label

PREBOOST™

MALE DESENSITIZING WIPES

Helps in temporarily
prolonging time until ejaculation

Developed by Dr. Harry Fisch
www.preboost.com

1 single-use premoistened towelette

Manufactured for 944 Corp
944 Park Ave, New York, NY 10028 www.preboost.com

PRINCIPAL DISPLAY PANEL – box label

PREBOOST™

MALE DESENSITIZING WIPES

Helps in temporarily prolonging time until ejaculation

10 single-use
premoistened towelette

Developed by Dr. Harry Fisch
|www.preboost.com